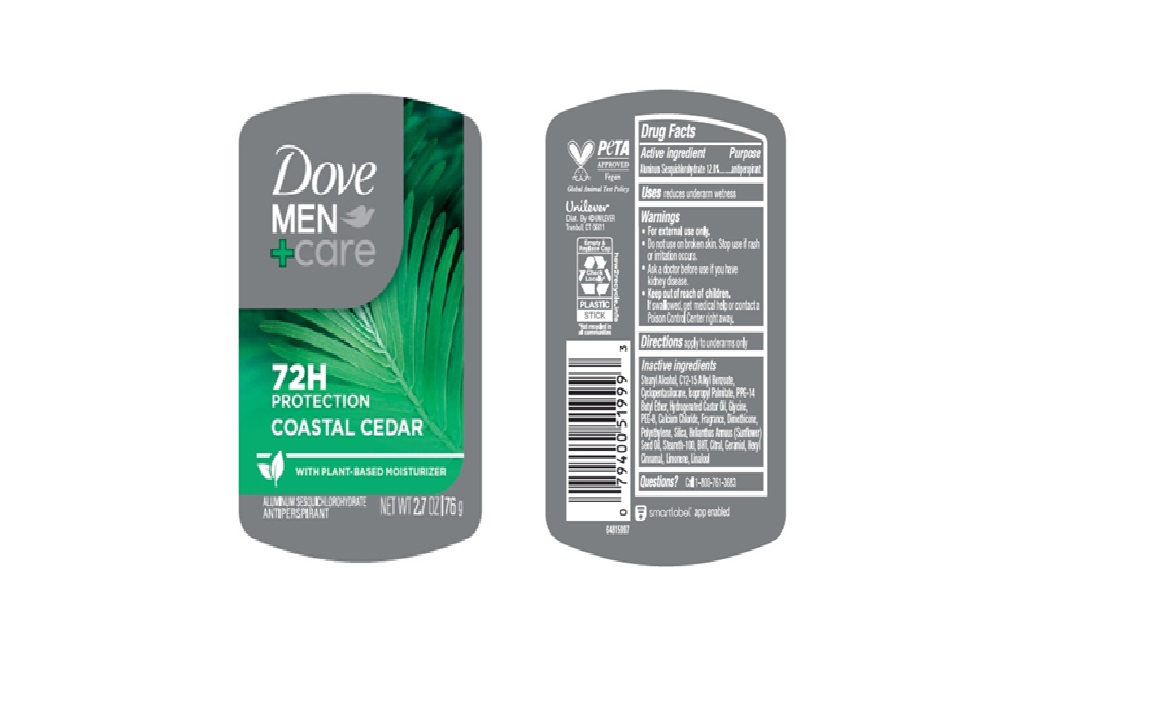 DRUG LABEL: Dove
NDC: 64942-2364 | Form: STICK
Manufacturer: Conopco d/b/a/ Unilever
Category: otc | Type: HUMAN OTC DRUG LABEL
Date: 20250331

ACTIVE INGREDIENTS: ALUMINUM SESQUICHLOROHYDRATE 12.8 g/100 g
INACTIVE INGREDIENTS: STEARYL ALCOHOL; PEG-8; SILICA; GERANIOL; LIMONENE, (+)-; CYCLOPENTASILOXANE; CALCIUM CHLORIDE; STEARETH-100; PPG-14 BUTYL ETHER; CITRAL; LINALOOL, (+/-)-; ISOPROPYL PALMITATE; HYDROGENATED CASTOR OIL; GLYCINE; POLYETHYLENE; HELIANTHUS ANNUUS (SUNFLOWER) SEED OIL; BHT; DIMETHICONE; C12-15 ALKYL BENZOATE; HEXYL CINNAMAL

Dove Men + Care Coastal Cedar 72H Antiperspirant

DESCRIPTION

Dove Men + Care Coastal Cedar 72H Antiperspirant

ACTIVE INGREDIENT

Aluminum Sesquichlorohydrate (12.8%)

PURPOSE

antiperspirant

INDICATIONS AND USAGE

reduces underarm wetness

WARNINGS

For external use only.

Do not use on broken skin.

Stop use if rash or irritation occurs.

Ask a doctor before use if you have kidney disease.

Keep out of reach of children. If swallowed, get medical help or contact a Poison Control Center right away

DOSAGE AND ADMINISTRATION

apply to underarms only

INACTIVE INGREDIENT

Stearyl Alcohol, C12-15 Alkyl Benzoate, Cyclopentasiloxane, Isopropyl Palmitate, PPG-14 Butyl Ether, Hydrogenated Castor Oil, Glycine, PEG-8, Calcium Chloride, Fragrance, Dimethicone, Polyethylene, Silica, Helianthus Annuus (Sunflower) Seed Oil, Steareth-100, BHT, Citral, Geraniol, Hexyl Cinnamal, Limonene, Linalool

QUESTIONS

Call 1-800-761-3683